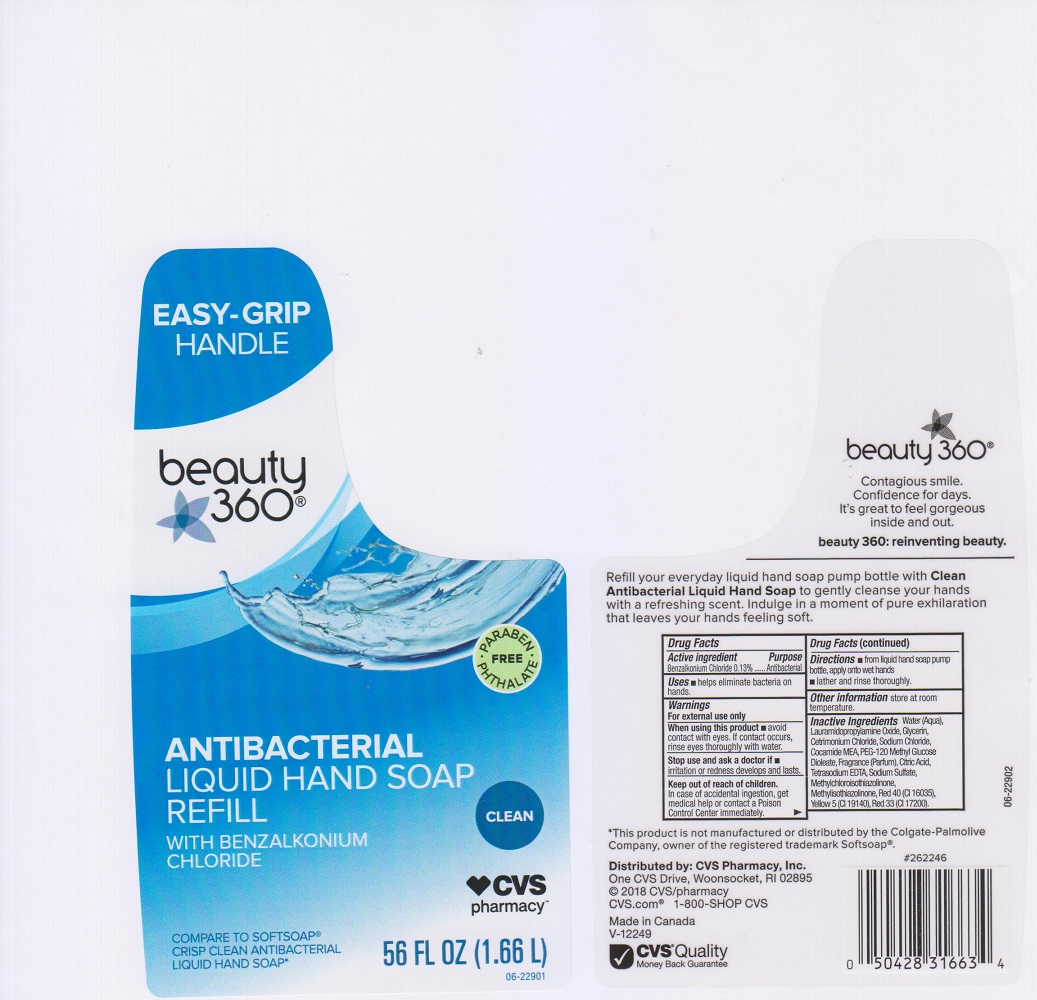 DRUG LABEL: CVS PHARMACY
NDC: 59779-325 | Form: LIQUID
Manufacturer: CVS PHARMACY
Category: otc | Type: HUMAN OTC DRUG LABEL
Date: 20200318

ACTIVE INGREDIENTS: BENZALKONIUM CHLORIDE 1.3 mg/1 mL
INACTIVE INGREDIENTS: WATER; CETRIMONIUM CHLORIDE; GLYCERIN; LAURAMIDOPROPYLAMINE OXIDE; COCO MONOETHANOLAMIDE; SODIUM CHLORIDE; PEG-120 METHYL GLUCOSE DIOLEATE; CITRIC ACID MONOHYDRATE; EDETATE SODIUM; SODIUM SULFATE; METHYLCHLOROISOTHIAZOLINONE; METHYLISOTHIAZOLINONE; FD&C RED NO. 40; FD&C YELLOW NO. 5; D&C RED NO. 33

DRUG FACTS

Active ingredient

Benzalkonium Chloride 0.13%

Purpose

Antibacterial

Uses

- helps eliminate bacteria on hands.

Warnings

For external use only

When using this product

- avoid contact with eyes. If contact occurs, rinse eyes thoroughly with water.

Stop use and ask a doctor if

- irritation or redness develops and lasts.

Keep out of reach of children.

In case of accidental ingestion, get medical help or contact a Poison Control Center immediately.

Directions

- apply onto wet hands.
- lather and rinse thoroughly.

Other information

store at room temperature.

Inactive ingredients

Water (Aqua), Cetrimonium Chloride, Glycerin, Lauramidopropylamine Oxide, Cocamide MEA, Sodium Chloride, PEG-120 Methyl Glucose Dioleate, Fragrance (Parfum), Citric Acid, Tetrasodium EDTA, Sodium Sulfate, Methylchloroisothiazolinone, Methylisothiazolinone, Red 40 (CI 16035), Yellow 5 (CI 19140), Red 33 (CI 17200).